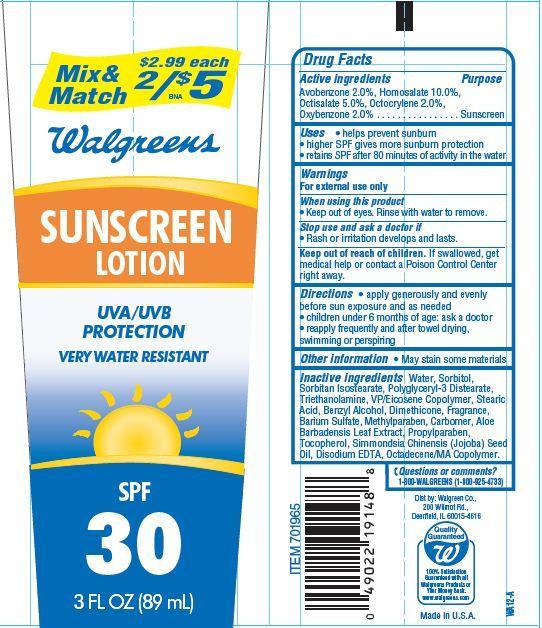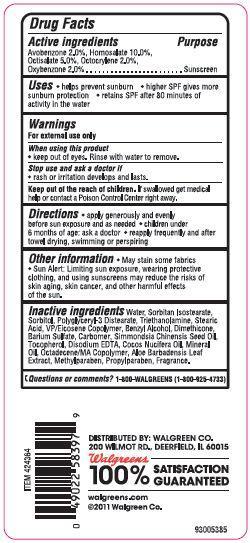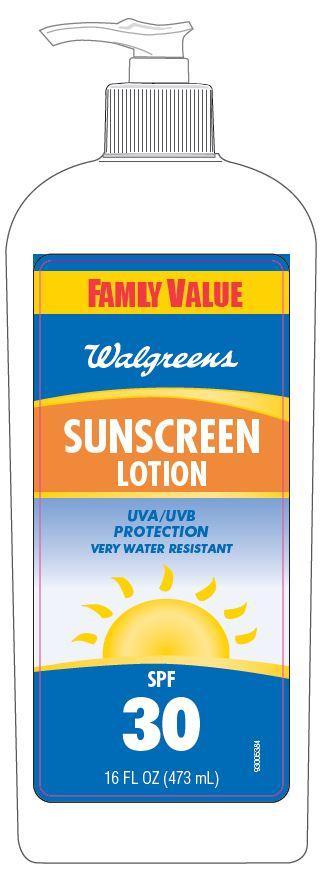 DRUG LABEL: Walgreens Sunscreen
NDC: 0363-4006 | Form: LOTION
Manufacturer: WALGREEN CO.
Category: otc | Type: HUMAN OTC DRUG LABEL
Date: 20121204

ACTIVE INGREDIENTS: AVOBENZONE 2 g/100 g; HOMOSALATE 10 g/100 g; OCTISALATE 5 g/100 g; OCTOCRYLENE 2 g/100 g; OXYBENZONE 2 g/100 g
INACTIVE INGREDIENTS: WATER; SORBITOL; STEARIC ACID; TROLAMINE; BARIUM SULFATE; BENZYL ALCOHOL; SORBITAN ISOSTEARATE; DIMETHICONE; METHYLPARABEN; TOCOPHEROL; EDETATE DISODIUM; PROPYLPARABEN; JOJOBA OIL; ALOE VERA LEAF

Drug Facts

Active Ingredients

Avobenzone 2.0 %

Homosalate 10.0%

Octisalate 5.0%

Octocrylene 2.0%

Oxybenzone 2.0%

Purpose

Sunscreen

Uses

- helps prevent sunburn
- higher SPF gives more sunburn protection
- retains SPF after 80 minutes of activity in the water

Warnings

For external use only

When using this product

- keep out of eyes. Rinse with water to remove.

stop use and ask a doctor if

- rash or irritation develops and lasts.

keep out of reach of children

If swallowed, get medical help or contact a Poison Control Center right away.

Directions

- apply generously and evenly before sun exposure and as needed
- children under 6 months of age:ask a doctor
- reapply frequently and after towel drying, swimming or perspiring.

Other Information

- May stain some materials

Inactive Ingredients

Water, Sorbitan Isostearate, Sorbitol, Polyglyceryl-3 Distearate, Triethanolamine, Stearic Acid, VP/Eicosene Copolymer, Benzyl Alcohol, Dimethicone, Barium Sulfate, Carbomer, Simmondsia Chinensis (Jojoba) Seed Oil, Tocopherol, Disodium EDTA, Cocos Nucifera (Coconut) Oil, Mineral Oil, Octadecene/MA Copolymer, Aloe Barbadensis Leaf Extract, Methylparaben, Propylparaben, Fragrance.

Principal Display Panel

Mix and
Match $2.99 each
2/$5
Walgreen
SUNSCREEN
LOTION
UVA/UVB
PROTECTION
VERY WATER RESISTANT
SPF
30
3 FL OZ (89 mL)
FAMILIY VALUE
Walgreens
SUNSCREEN
LOTION
UVA/UVB
PROTECTION
VERY WATER RESISTANT
SPF
30
16 FL OZ (473 mL)